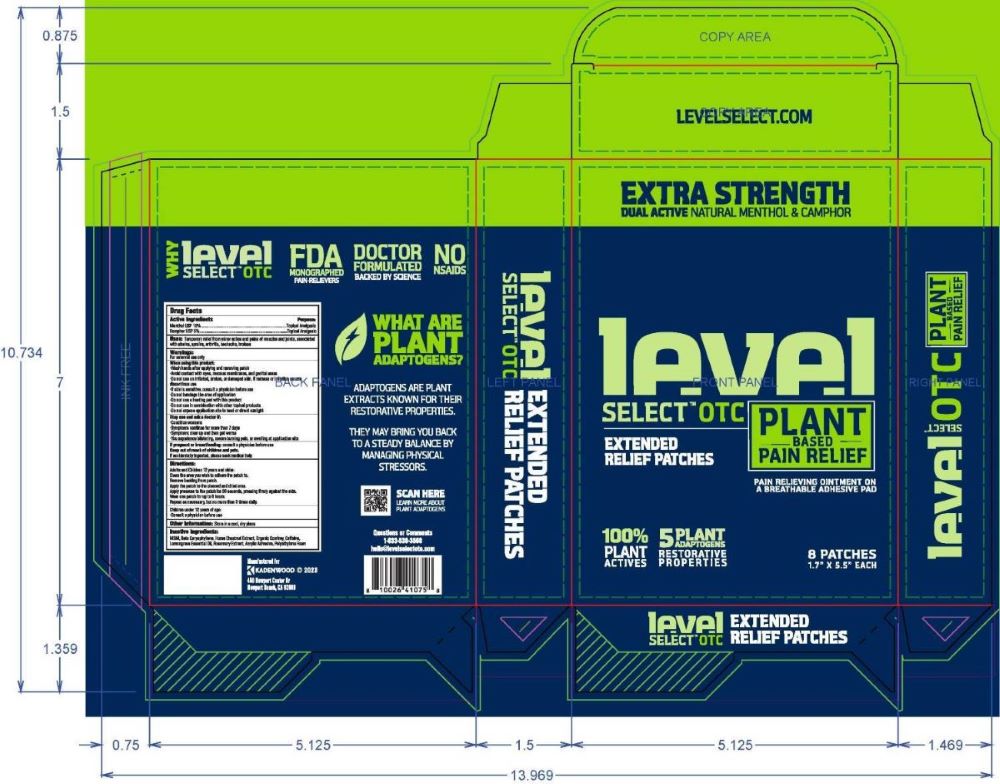 DRUG LABEL: Level Select Menthol Camphor Patch
NDC: 83191-004 | Form: PATCH
Manufacturer: Kadenwood LLC
Category: otc | Type: HUMAN OTC DRUG LABEL
Date: 20241228

ACTIVE INGREDIENTS: MENTHOL 10 mg/100 mg; CAMPHOR (SYNTHETIC) 5 mg/100 mg
INACTIVE INGREDIENTS: LOW DENSITY POLYETHYLENE; CAFFEINE; HORSE CHESTNUT; ROSEMARY OIL; EAST INDIAN LEMONGRASS OIL; DIMETHYL SULFONE; COMFREY; CARYOPHYLLENE

Level Select 10% Menthol, 5% Camphor

OTC-ACTIVE INGREDIENTS

Menthol 10%

Camphor 5%

OTC-PURPOSE

Topical Analgesic

Uses

Temporary relief from minor aches and pains of muscles and joints, associated with strains, sprains, arthritis, backache, bruises

Warnings

For external use only

When using this product:

- Wash hands after applying and removing patch
- Avoid contact with eyes, mucous membranes, and genital areas
- Do not use on irritated, broken, or damaged skin. If redness or irritation occurs discontinue use.
- If skin is sensitive, consult a physician before use
- Do not bandage the area of application
- Do not use a heating pad with this product
- Do not use in combination with other topical products
- Do not expose applicaton site to heat or direct sunlight

Stop use and ask a doctor if:

- Condition worsens
- Symptoms continue for more than 7 days
- Symptoms clear up and then get worse
- You experience blistering, severe burning pain, or swelling at applicaton site

If pregnant or breastfeeding:

consult a physician before use

Keep out of reach of chlidren and pets

If accidentally ingested, please seek medical help

Directions:

Adults and Children 12 years and older:

Clean the area you wish to adhere the patch to.

Remove backing from the patch

Apply the patch to the cleaned and dried area.

Apply pressure to the patch for 30 seconds, pressing firmly against the skin.

Wear one patch for up to 8 hours

Repeat as necessary, but no more than 3 times daily

Children under 12 years of age:

- Consult a physician before use

Other Information:

Store in a cool, dry place

Inactive Ingredients:

MSM, Beta Caryophylene, Horse Chestnut Extract, Organic Comfrey, Caffeine, Lemongrass Essential Oil, Rosemary Extract, Acrylic Adhesive, Polyethylene Foam